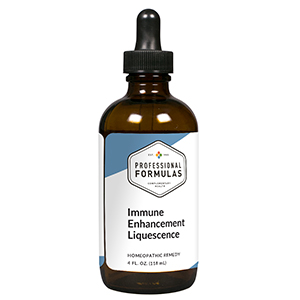 DRUG LABEL: Immune Enhancement Liquescence
NDC: 63083-3029 | Form: LIQUID
Manufacturer: Professional Complementary Health Formulas
Category: homeopathic | Type: HUMAN OTC DRUG LABEL
Date: 20190815

ACTIVE INGREDIENTS: ECHINACEA ANGUSTIFOLIA WHOLE 2 [hp_X]/118 mL; ECHINACEA PURPUREA WHOLE 2 [hp_X]/118 mL; POPULUS BALSAMIFERA LEAF BUD 2 [hp_X]/118 mL; GOLDENSEAL 5 [hp_X]/118 mL; CINCHONA OFFICINALIS BARK 6 [hp_X]/118 mL; CALCIUM SULFIDE 6 [hp_X]/118 mL; IODINE 6 [hp_X]/118 mL; POTASSIUM DICHROMATE 6 [hp_X]/118 mL; MERCURIUS SOLUBILIS 12 [hp_X]/118 mL
INACTIVE INGREDIENTS: ALCOHOL; WATER

T29

ACTIVE INGREDIENTS

Echinacea angustifolia 2X
Echinacea purpurea 2X
Populus candicans 2X
Hydrastis canadensis 5X
Cinchona officinalis 6X
Hepar sulphuris calcareum 6X
Iodium 6X
Kali bichromicum 6X
Mercurius solubilis 12X

QUESTIONS

Professional Formulas

PO Box 2034 Lake Oswego, OR 97035

INDICATIONS

For the temporary relief of minor aches, pains, or inflammation in the muscles or joints, sinus or nasal congestion, sore throat, hoarseness, chills, occasional headache, nausea, fatigue, or debility.*

PURPOSE

*Claims based on traditional homeopathic practice, not accepted medical evidence. Not FDA evaluated.

WARNINGS

Persistent symptoms may be a sign of a serious condition. If symptoms persist or are accompanied by a fever, rash, or persistent headache, consult a doctor. Keep out of the reach of children. In case of overdose, get medical help or contact a poison control center right away. If pregnant or breastfeeding, ask a healthcare professional before use.

Keep out of the reach of children.

PREGNANCY OR BREAST FEEDING

If pregnant or breastfeeding, ask a healthcare professional before use.

DIRECTIONS

Place drops under tongue 30 minutes before/after meals. Adults and children 12 years and over: Take one full dropper up to 2 times per day. Consult a physician for use in children under 12 years of age.

OTHER INFORMATION

Tamper resistant. If seal is broken, do not use. After opening, close container tightly and store at room temperature away from heat.

INACTIVE INGREDIENTS

20% ethanol, purified water.

LABEL

Est 1985

Professional Formulas

Complementary Health

Immune Enhancement Liquescence

Homeopathic Remedy

4 FL. OZ. (118 mL)